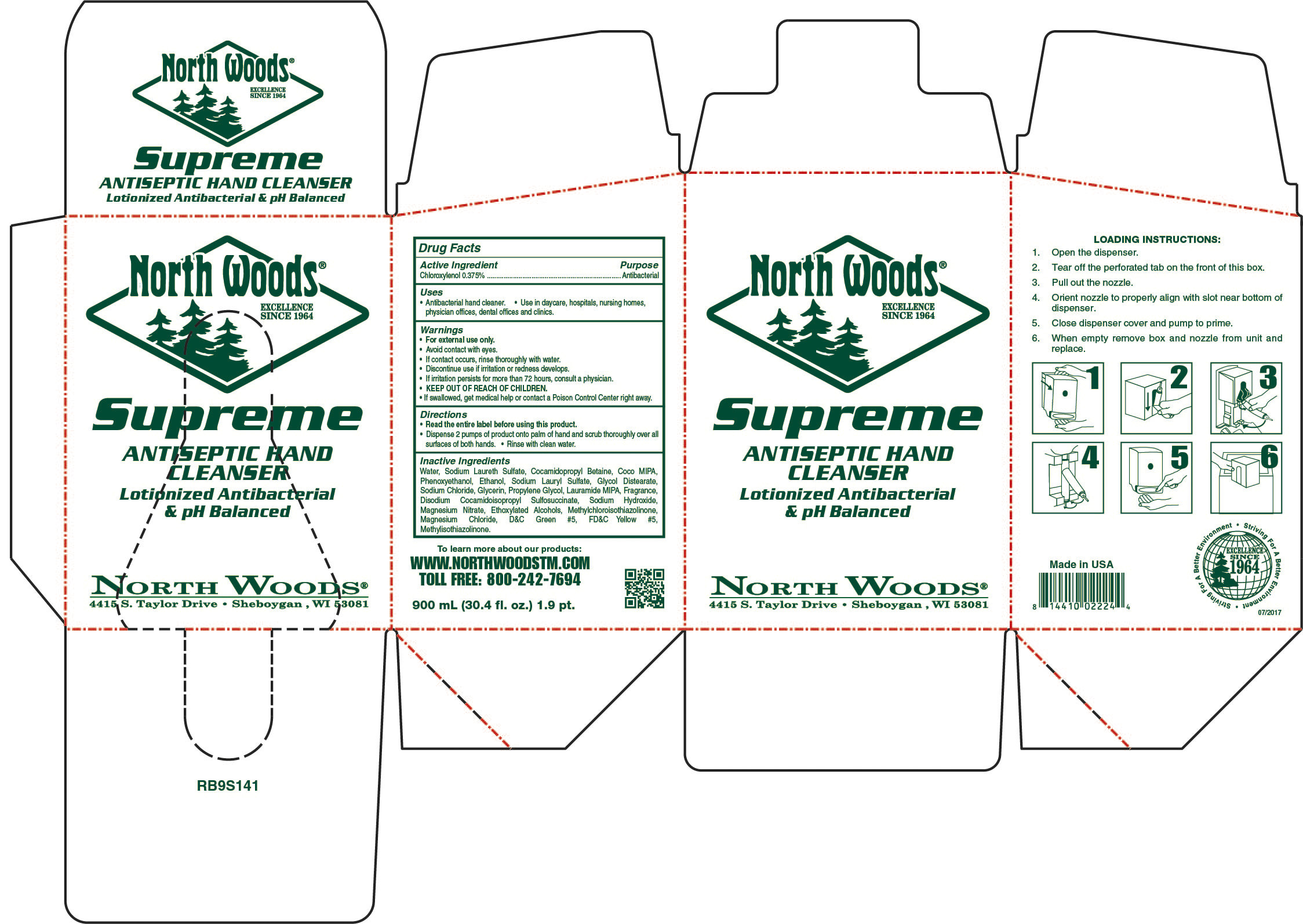 DRUG LABEL: North Woods Supreme Antiseptic Hand Cleanser
NDC: 53125-708 | Form: SOAP
Manufacturer: Superior Chemical Corporation
Category: otc | Type: HUMAN OTC DRUG LABEL
Date: 20241223

ACTIVE INGREDIENTS: CHLOROXYLENOL 3.75 mg/1 mL
INACTIVE INGREDIENTS: WATER; SODIUM LAURYL SULFATE; COCO DIETHANOLAMIDE; COCAMIDOPROPYL BETAINE; PHENOXYETHANOL; PROPYLENE GLYCOL; DIMETHYL BENZYL CARBINYL BUTYRATE; MAGNESIUM NITRATE; LAURIC DIETHANOLAMIDE; BENZYL BENZOATE; D&C GREEN NO. 5; FD&C YELLOW NO. 5; ETHYL ACETOACETATE; DIMETHYL BENZYL CARBINYL ACETATE; SODIUM CARBONATE; .GAMMA.-DECALACTONE; ETHYL METHYLPHENYLGLYCIDATE; METHYL ANTHRANILATE; SODIUM HYDROXIDE; SODIUM ALUMINIUM SILICATE; CALCIUM SILICATE; SODIUM FERROCYANIDE; LAURIC ISOPROPANOLAMIDE; GLYCOL DISTEARATE; METHYL ALCOHOL; ETHYLENE OXIDE; LINALOOL, (+/-)-; CHLOROACETIC ACID; ETHYL BUTYRATE; MYRCENE; DIOXANE; TRIBASIC CALCIUM PHOSPHATE; METHYLCHLOROISOTHIAZOLINONE; METHYLISOTHIAZOLINONE

North Woods Supreme Antiseptic Hand Cleanser

North Woods Supreme Antiseptic Hand Cleanser

Active Ingredient

Chloroxylenol 0.375%

North Woods Supreme Antiseptic Hand Cleanser

Uses

- Antibacterial hand cleaner.
- Use in daycare, hospitals, nursing homes, physicians offices, dental offices and clinics

North Woods Supreme Antiseptic Hand Cleanser

Warnings

- For external use only.
- Avoid contact with eyes.
- Children under the age of 6 should be supervised by an adult when using this product.
- Discontinue use is irritation or redness develops.
- If irritation persists for more than 72 hours, consult a physician.
- KEEP OUT OF REACH OF CHILDREN.

North Woods Supreme Antiseptic Hand Cleanser

Directions

- Read the entire label before using this product.
- Dispense 1-2 pumps of product onto wet palm.
- Lather and rinse hands with clean water

North Woods Supreme Antiseptic Hand Cleanser

Inactive Ingredients

Water, Sodium Lauryl lSulfate, Cocamide DEA, Cocamidopropyl betadine, Phenoxyethanol, Sodium Laureth Sulfate, Propylene Glycol, Fragrance, DMDM Hydantoin, Glycol Stearate, Laurimide DEA, Glycerine, Tocopheryl Acetate, D&C Green #5, FD&C Yellow #5.

North Woods Supreme Antiseptic Hand Cleanser

Questions or Comments? Phone: (800) 777-9343

MDS information:(800) 891-4965

North Woods Supreme Antiseptic Hand Cleanser

Purpose

Antibacterial

North Woods Supreme Antiseptic Hand Cleanser

KEEP OUT OF REACH OF CHILDREN

North Woods by Superior Supreme Antiseptic Hand Cleanser

SUperior 141

North Woods by Superior Supreme Antiseptic Hand Cleanser

Lotionized Antibacterial and pH Balanced

Excellence Since 1964

Superior Chemical Corporation

Sheboygan, WI 53081